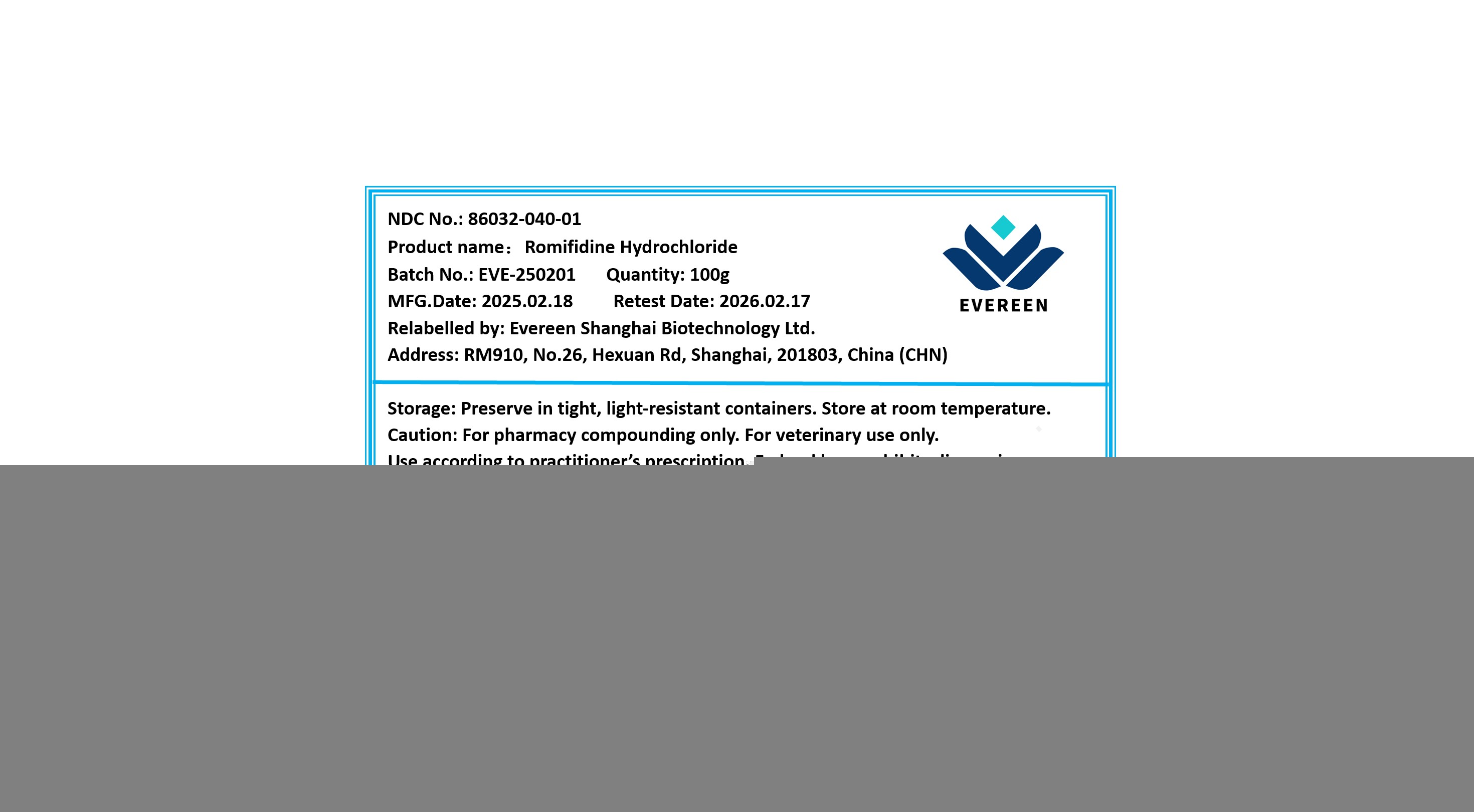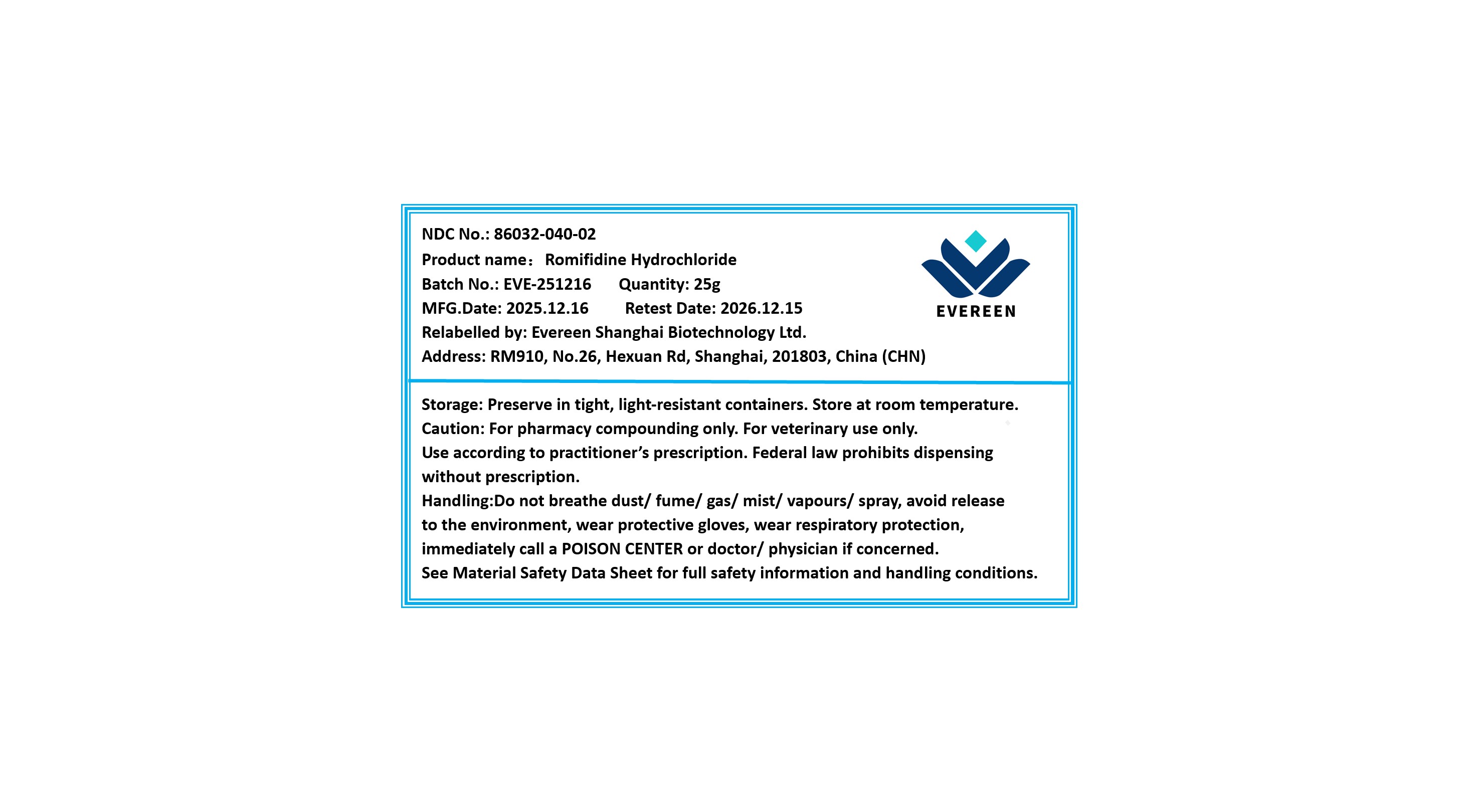 DRUG LABEL: Romifidine Hydrochloride
NDC: 86032-040 | Form: POWDER
Manufacturer: Evereen Shanghai Biotechnology Ltd.
Category: other | Type: BULK INGREDIENT - ANIMAL DRUG
Date: 20260211

ACTIVE INGREDIENTS: ROMIFIDINE 1 g/1 g

Romifidine Hydrochloride